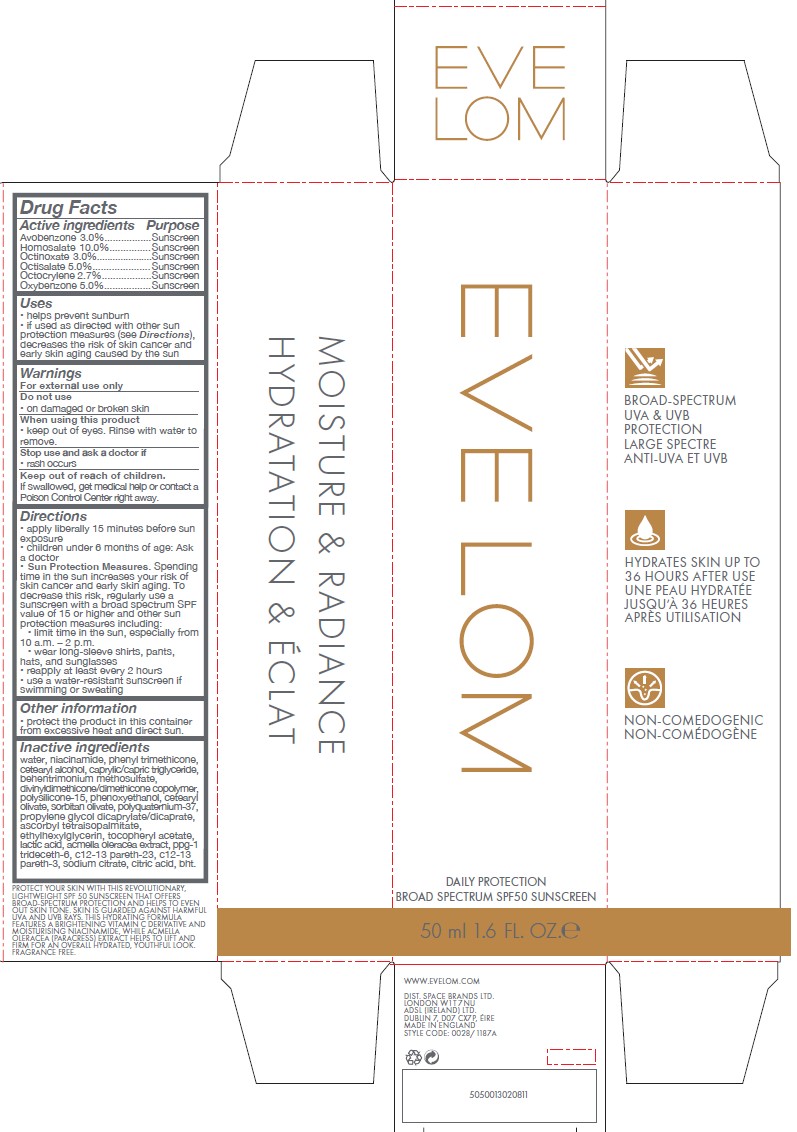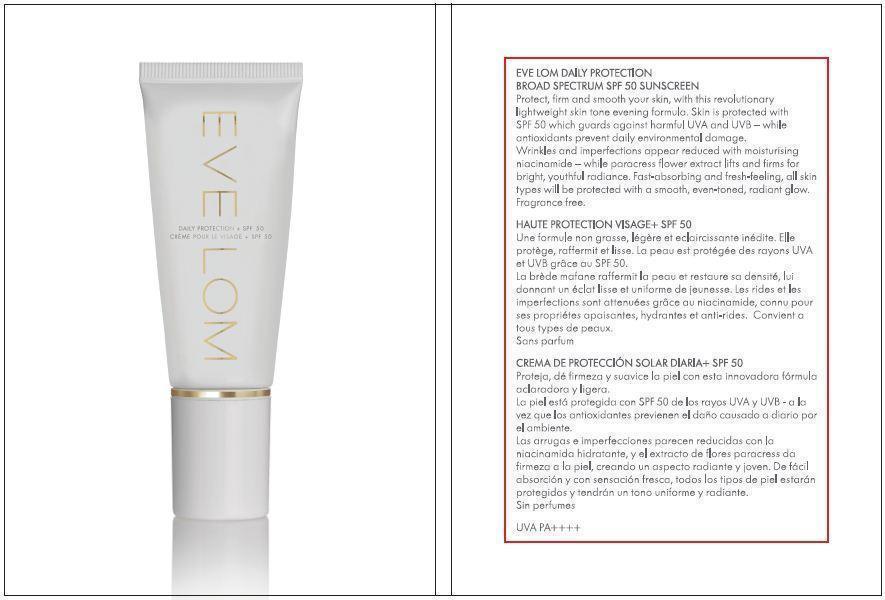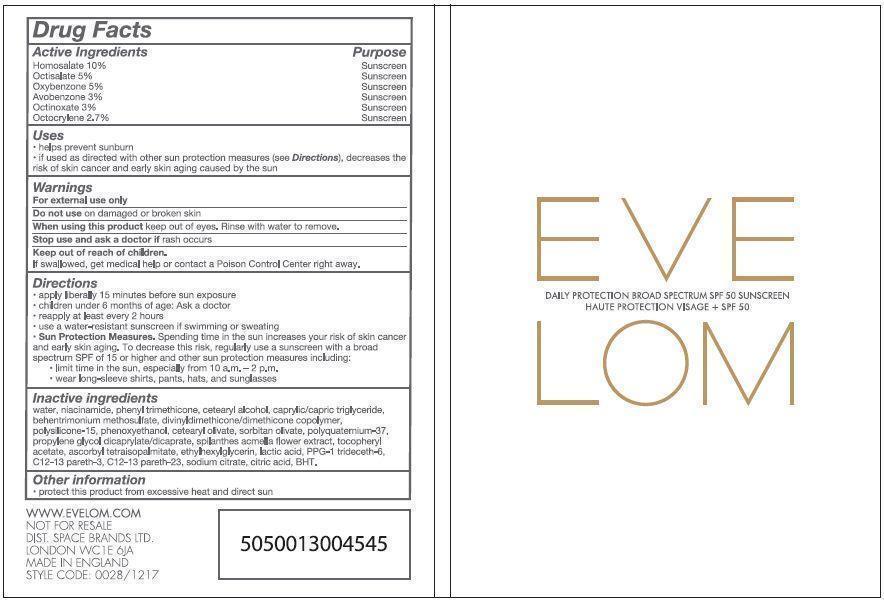 DRUG LABEL: Eve Lom Daily Protection Broad Spectrum SPF 50 Sunscreen
NDC: 61601-1217 | Form: CREAM
Manufacturer: Space Brands Limited
Category: otc | Type: HUMAN OTC DRUG LABEL
Date: 20250924

ACTIVE INGREDIENTS: HOMOSALATE 0.5 g/5 mL; OCTISALATE 0.25 g/5 mL; OXYBENZONE 0.25 g/5 mL; AVOBENZONE 0.15 g/5 mL; OCTINOXATE 0.15 g/5 mL; OCTOCRYLENE 0.135 g/5 mL
INACTIVE INGREDIENTS: WATER; NIACINAMIDE; PHENYL TRIMETHICONE; MEDIUM-CHAIN TRIGLYCERIDES; CETOSTEARYL ALCOHOL; BEHENTRIMONIUM METHOSULFATE; POLYSILICONE-15; PHENOXYETHANOL; CETEARYL OLIVATE; SORBITAN OLIVATE; POLYQUATERNIUM 37 (200 MPA.S); PROPYLENE GLYCOL DICAPRYLATE/DICAPRATE; .ALPHA.-TOCOPHEROL ACETATE; ACMELLA OLERACEA FLOWER; ASCORBYL TETRAISOPALMITATE; ETHYLHEXYLGLYCERIN; LACTIC ACID; PPG-1 TRIDECETH-6; C12-13 PARETH-3; C12-13 PARETH-23; SODIUM CITRATE; CITRIC ACID MONOHYDRATE; BUTYLATED HYDROXYTOLUENE

Eve Lom® Daily Protection Broad Spectrum SPF 50 Sunscreen

Drug Facts

Active Ingredients Purpose

Homosalate 10% Sunscreen

Octisalate 5% Sunscreen

Oxybenzone 5% Sunscreen

Avobenzone 3% Sunscreen

Octinoxate 3% Sunscreen

Octocrylene 2.7% Sunscreen

Uses

- helps prevent sunburn
- if used as directed with other sun protection measures (see Directions), decreases the risk of skin cancer and early skin aging caused by the sun

Warnings

For external use only

Do not use on damaged or broken skin

WHEN USING

When using this productkeep out of eyes. Rinse with water to remove.

Stop use and ask a doctor ifrash occurs.

Keep out of reach of children.

If swallowed, get medical help or contact a Poison Control Center right away.

Directions

- apply liberally 15 minutes before sun exposure
- children under 6 months of age: Ask a doctor
- reapply at least every 2 hours
- use a water-resistant sunscreen if swimming or sweating
- Sun Protection Measures.Spending time in the sun increases your risk of skin cancer and early skin aging. To decrease this risk, regularly use a sunscreen with a broad spectrum SPF iof 15 or higher and other sun protection measures including:

- limit time in the sun, especially from 10 a.m. - 2 p.m.

- wear long-sleeve shirts, pants, hats, and sunglasses

Inactive ingredients

water, niacinamide, phenyl trimethicone, cetearyl alcohol, caprylic/capric triglyceride, behentrimonium methosulfate, divinyldimethicone/dimethicone copolymer, polysilicone-15, phenoxyethanol, cetearyl olivate, sorbitan olivate, polyquaternium-37, propylene glycol dicaprylate/dicaprate, spilanthes acmella flower extract, tocopheryl acetate, ascorbyl tetraisopalmitate, ethylhexylglycerin, lactic acid, PPG-1 trideceth-6, C12-13 pareth-3, C12-13 pareth-23, sodium citrate, citric acid, BHT.

Other information

- protect this product from excessive heat and direct sun

PRINCIPAL DISPLAY/OUTSIDE PANEL - 5 mL Wallet Sachet

EVE LOM

DAILY PROTECTION

BROAD SPECTRUM SPF 50 SUNSCREEN

5ml 0.169 FL.OZ. e

PACKAGE LABEL

EVE LOM

DAILY PROTECTION

BROAD SPECTRUM SPF 50 SUNSCREEN

50 ml 1.6 Fl. Oz. E